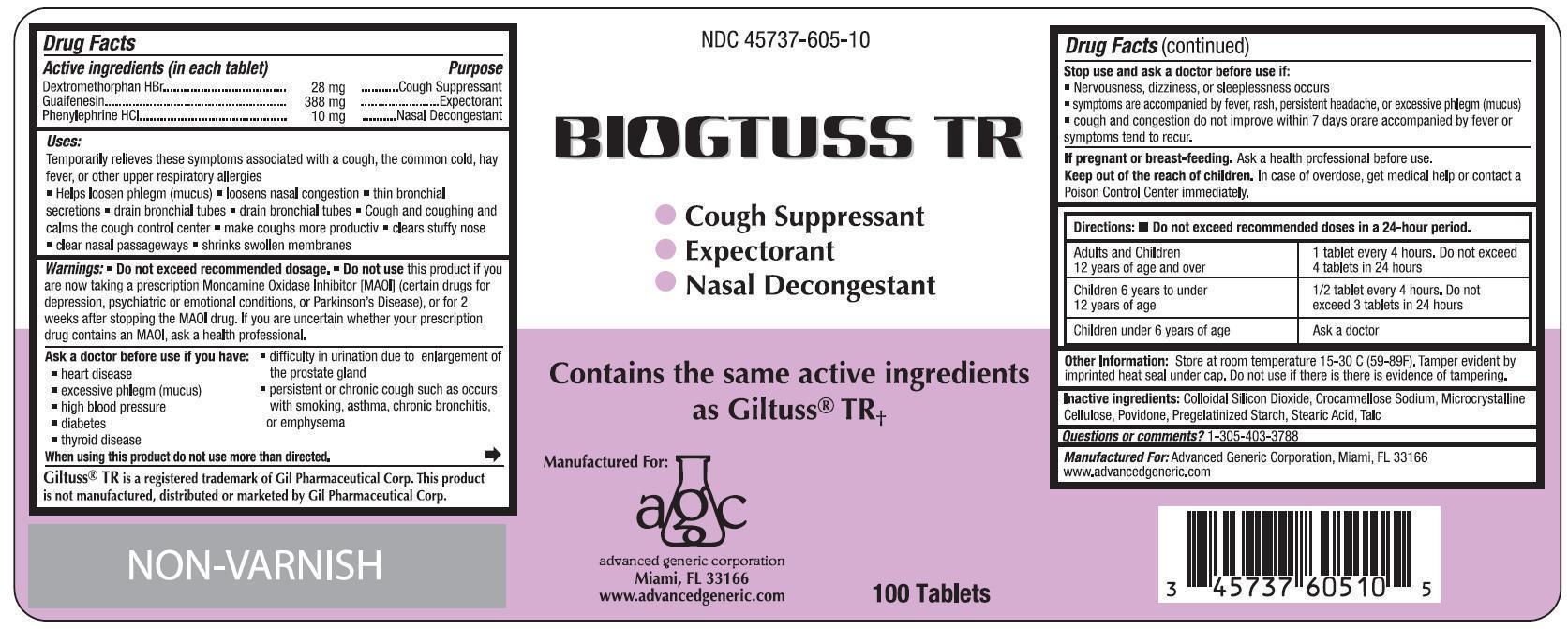 DRUG LABEL: Biogtuss
NDC: 45737-605 | Form: TABLET
Manufacturer: Advanced Generic Corporation
Category: otc | Type: HUMAN OTC DRUG LABEL
Date: 20241220

ACTIVE INGREDIENTS: GUAIFENESIN 388 mg/1 1; PHENYLEPHRINE HYDROCHLORIDE 10 mg/1 1; DEXTROMETHORPHAN HYDROBROMIDE 28 mg/1 1
INACTIVE INGREDIENTS: SILICON DIOXIDE; CARBOXYMETHYLCELLULOSE SODIUM; CELLULOSE, MICROCRYSTALLINE; POVIDONE; STARCH, CORN; STEARIC ACID; TALC

AGC-BioGTussTR 605

Active ingredients (in each tablet) Purpose

Dextromethorphan HBR .... 28 mg ............ Cough Suppressant

Guaifenesin ..................... 388 mg ........... Expectorant

Phenylephrine HCl ............ 10 mg .......... Nasal Decongestant

Purpose

Cough Suppressant

Expectorant

Nasal Decongestant

Uses

Temporarily relieves these symptoms associated with a cough, the common cold, hay fever, or other upper respiratory allergies

- helps loosen phlegm (mucus)
- loosens nasal congestion
- thin bronchial secretions
- drain bronchial tubes
- cough and coughing and calms the cough control center
- make coughs more productive
- clears stuffy nose
- clear nasal passageways
- shrinks swollen membranes

Warnings

Do not exceed recommended dosage

Do not use this product if you are taking a Monoamine Oxidase Inhibitor (MAOI) (certain drugs for depression, psychiatric or emotional conditions, or Parkinson's Disease), or for 2 weeks after stopping the MAOI drug. If you are uncertain whether your prescription drug contains an MAOI, ask a health professional.

Ask a doctor before use if you have:

- heart disease
- excessive phlegm (mucus)
- high blood pressure
- diabetes
- thyroid disease
- difficulty in urination due to enlargement of the prostate gland
- persistent or chronic cough such as occurs with smoking, asthma, chronic bronchitis, or emphysema

When using this product do not use more than directed

Stop use and ask a doctor if:

- Nervousness, dizziness, or sleeplessness occurs
- symptoms are accompanied by fever, rash, persistent headache, or excessive phlegm (mucus)
- cough and congestion do not improve within 7 days or are accompanied by fever or symptoms tend to recur.

PREGNANCY OR BREAST FEEDING

If pregnant or breast-feeding.Ask a health professional before use.

KEEP OUT OF REACH OF CHILDREN

Keep out of the reach of children. In case of overdose, get medical help or contact a Poison Control Center immediately.

DOSAGE AND ADMINISTRATION

Directions: Do not exceed recommended doses in a 24-hour period

Adults and children 12 years of age and over 1 tablet every 4 hours. Do not exceed 4 tablets in 24 hours

Children 6 to 12 years of age 1/2 tablet every 4 hours. Do not exceed 3 tablets in 24 hours

Children under 6 years of age Ask a doctor

INACTIVE INGREDIENT

Inactive ingredients:Colloidal silicon dioxide, crocarmellose sodium, microcrystalline cellulose, povidone, pregelatinized starch, stearic acid, talc

Questions or comments?305-403-3788